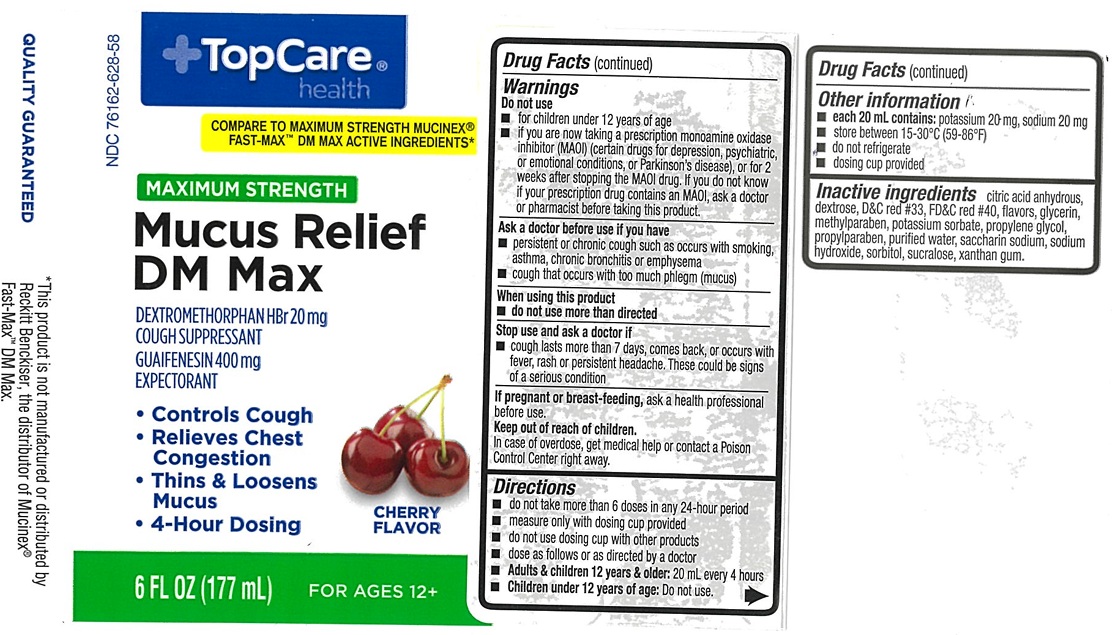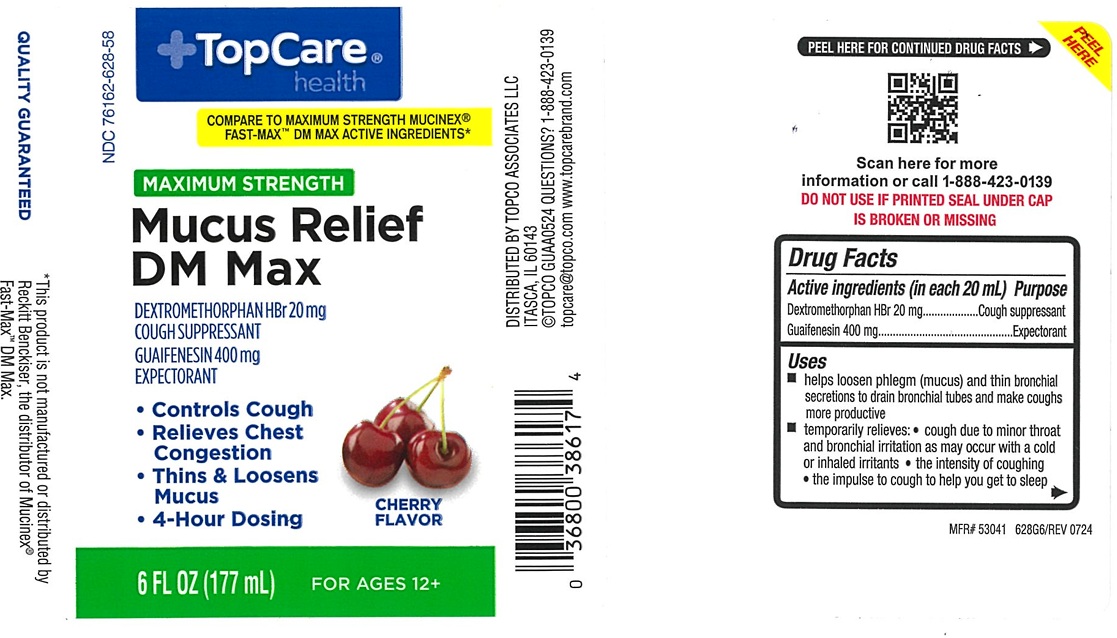 DRUG LABEL: Maximum Strength Mucus Relief DM Max
NDC: 76162-628 | Form: LIQUID
Manufacturer: Topco Associates, LLC
Category: otc | Type: Human OTC Drug Label
Date: 20250212

ACTIVE INGREDIENTS: DEXTROMETHORPHAN HYDROBROMIDE 20 mg/20 mL; GUAIFENESIN 400 mg/20 mL
INACTIVE INGREDIENTS: ANHYDROUS CITRIC ACID; D&C RED NO. 33; DEXTROSE, UNSPECIFIED FORM; FD&C RED NO. 40; GLYCERIN; METHYLPARABEN; POTASSIUM SORBATE; PROPYLENE GLYCOL; PROPYLPARABEN; WATER; SACCHARIN SODIUM; SODIUM HYDROXIDE; SORBITOL; SUCRALOSE; XANTHAN GUM

Maximum Strength Mucus Relief DM Max 628

ACTIVE INGREDIENTS (in each 20 mL)

Dextromethorphan HBr, 20 mg

Guaifenesin, 400 mg

PURPOSE

Cough Suppressant

Expectorant

USE(S)

- helps loosen phlegm (mucus) and thin bronchial secretions to drain bronchial tubes and make coughs more productive
- temporarily relieves:
- cough due to minor throat and bronchial irritation as may occur with a cold or inhaled irritants
- the intensity of coughing
- the impulse to cough to help you get to sleep

WARNINGS

.

DO NOT USE

- for children under 12 years of age
- if you are now taking a prescription monoamine oxidase inhibitor (MAOI) (certain drugs for depression, psychiatric, or emotional conditions, or Parkinson's disease), or for 2 weeks after stopping the MAOI drug. If you do not know if your prescription drug contains an MAOI, ask a doctor or pharmacist before taking this product.

ASK A DOCTOR BEFORE USE IF

- persistent or chronic cough such as occurs with smoking, asthma, chronic bronchitis or emphysema
- cough that occurs with too much phlegm (mucus)

WHEN USING THIS PRODUCT

do not use more than directed

STOP USE AND ASK DOCTOR IF

- cough lasts more than 7 days, comes back, or occurs with fever, rash, or persistent headache. These could be signs of a serious condition.

IF PREGNANT OR BREAST-FEEDING

ask a health professional before use.

KEEP OUT OF REACH OF CHILDREN

In case of overdose, get medical help or contact a Poison Control Center right away.

DIRECTIONS

- do not take more than 6 doses in any 24-hour period
- measure only with dosing cup provided
- do not use dosing cup with other products
- dose as follows or as directed by a doctor
- Adults & children 12 years & older: 20 mL every 4 hours
- Children under 12 years of age: Do not use

OTHER INFORMATION

- each 20 mL contains: potassium 20 mg, sodium 20 mg
- store between 15-30°C (59-86°F)
- do not refrigerate
- dosing cup provided

INACTIVE INGREDIENTS

citric acid anhydrous, dextrose, D&C red # 33, FD&C Red #40, flavors, glycerin, methylparaben, potassium sorbate, propylene glycol, propylparaben, purified water, saccharin sodium, sodium hydroxide, sorbitol, sucralose, xanthan gum

PACKAGE LABEL.PRINCIPAL DISPLAY PANEL

TopCare® health

NDC 76162-628-58

COMPARE TO MAXIMUM STRENGTH MUCINEX® FAST-MAX™ DM MAX ACTIVE INGREDIENTS*

MAXIMUM STRENGTH

Mucus Relief

DM Max

DEXTROMETHORPHAN HBr 20 mg

COUGH SUPPRESSANT
GUAIFESNESIN 400 mg

EXPECTORANT

- Controls Cough
- Relieves Chest Congestion
- Thins & Loosens Mucus
- 4-Hour Dosing

CHERRY FLAVOR

6 FL OZ (177 mL) FOR AGES 12+